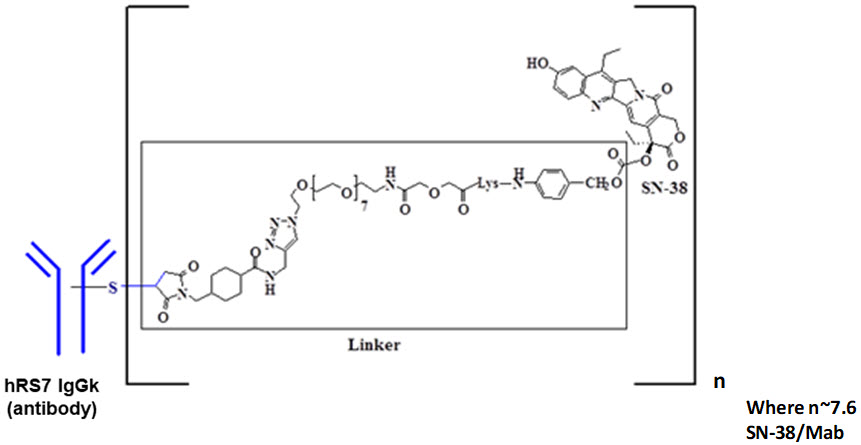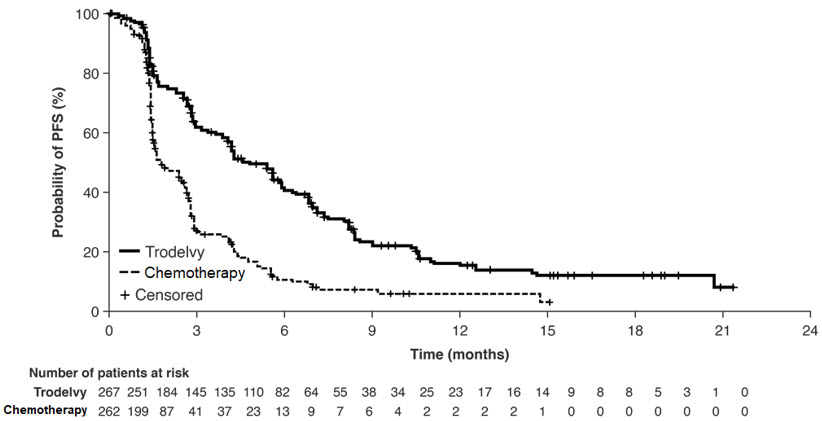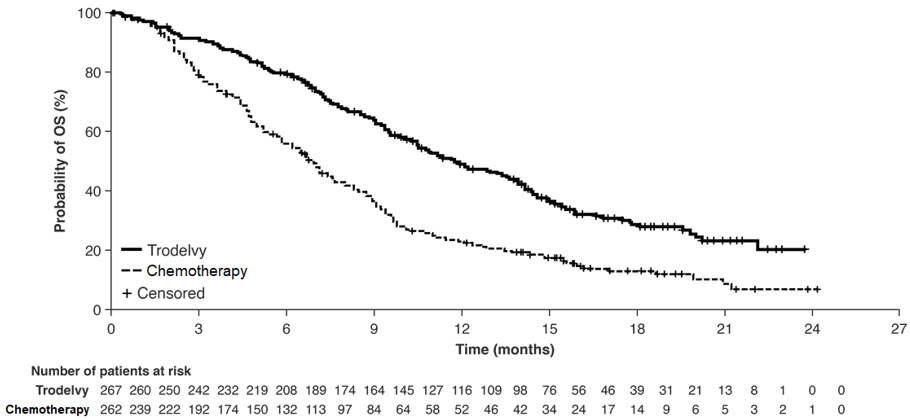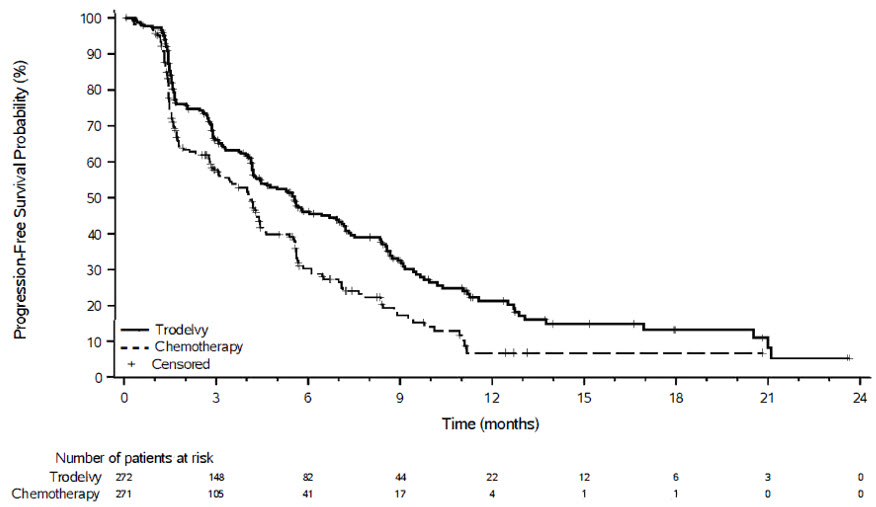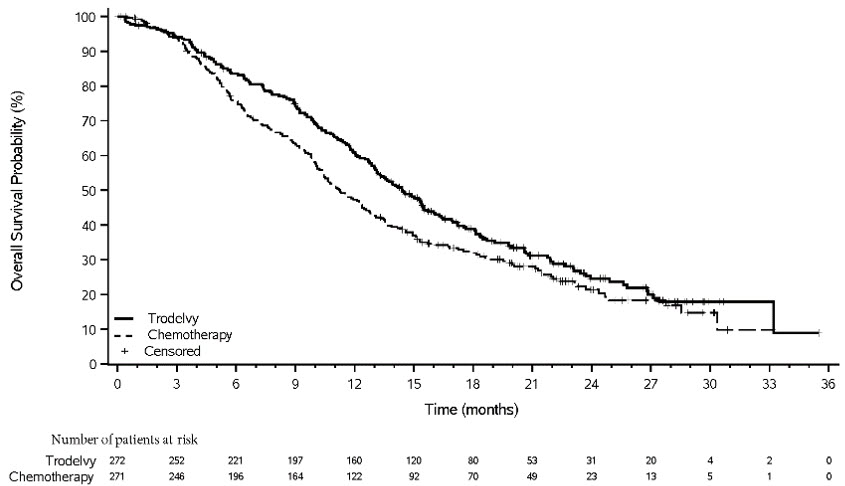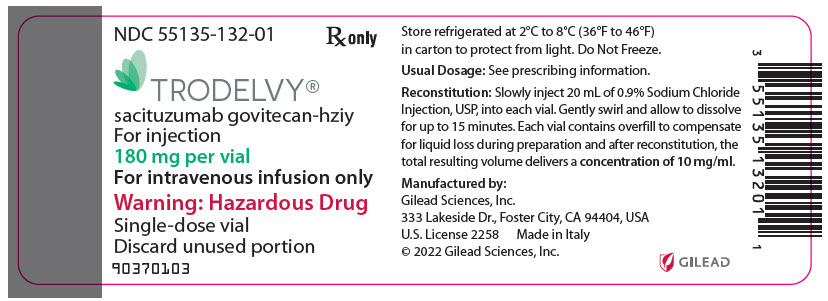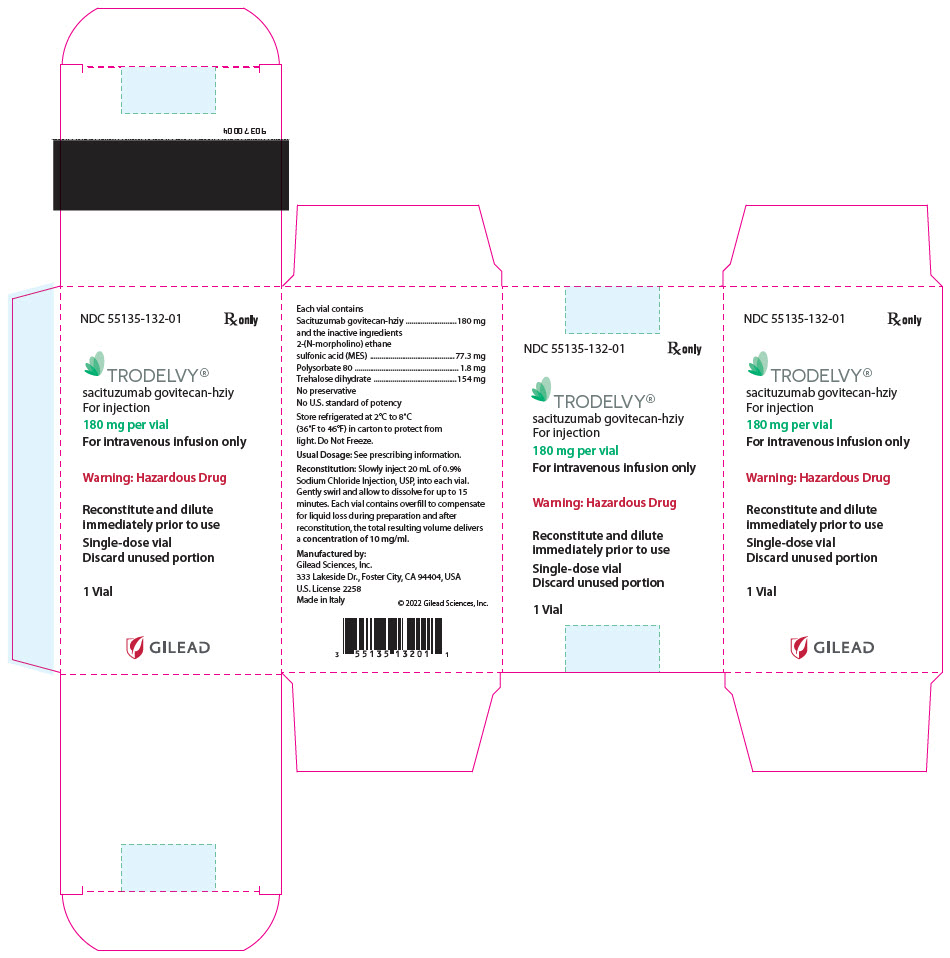 DRUG LABEL: TRODELVY
NDC: 55135-132 | Form: POWDER, FOR SOLUTION
Manufacturer: Gilead Sciences, Inc.
Category: prescription | Type: HUMAN PRESCRIPTION DRUG LABEL
Date: 20250331

ACTIVE INGREDIENTS: SACITUZUMAB GOVITECAN 180 mg/1 1
INACTIVE INGREDIENTS: 2-(N-morpholino)ethanesulfonic acid; trehalose; polysorbate 80

HIGHLIGHTS OF PRESCRIBING INFORMATION

These highlights do not include all the information needed to use TRODELVY safely and effectively. See full prescribing information for TRODELVY
TRODELVY® (sacituzumab govitecan-hziy) for injection, for intravenous use
Initial U.S. Approval: 2020

WARNING: NEUTROPENIA AND DIARRHEA

See full prescribing information for complete boxed warning.

TRODELVY can cause severe, life-threatening, or fatal neutropenia. Withhold TRODELVY for absolute neutrophil count below 1500/mm^3 or neutropenic fever. Monitor blood cell counts periodically during treatment. Primary prophylaxis with G-CSF is recommended for all patients at increased risk of febrile neutropenia. Initiate anti-infective treatment in patients with febrile neutropenia without delay. (2.3, 5.1)

TRODELVY can cause severe diarrhea. Monitor patients with diarrhea and give fluid and electrolytes as needed. At the onset of diarrhea, evaluate for infectious causes and, if negative, promptly initiate loperamide. If severe diarrhea occurs, withhold TRODELVY until resolved to ≤ Grade 1 and reduce subsequent doses. (2.3, 5.2)

RECENT MAJOR CHANGES

Boxed Warning | 03/2025
Indications and Usage, Locally Advanced or Metastatic Urothelial Cancer – Accelerated Approval (text removed) (1.2) | 11/2024
Dosage and Administration (2.2, 2.3, 2.4) | 03/2025
Warnings and Precautions (5.1) | 03/2025

1 INDICATIONS AND USAGE

TRODELVY is a Trop-2-directed antibody and topoisomerase inhibitor conjugate indicated for the treatment of adult patients with:

Locally Advanced or Metastatic Breast Cancer

- Unresectable locally advanced or metastatic triple-negative breast cancer (mTNBC) who have received two or more prior systemic therapies, at least one of them for metastatic disease. (1.1, 14.1)
- Unresectable locally advanced or metastatic hormone receptor (HR)-positive, human epidermal growth factor receptor 2 (HER2)-negative (IHC 0, IHC 1+ or IHC 2+/ISH–) breast cancer who have received endocrine-based therapy and at least two additional systemic therapies in the metastatic setting. (1.1, 14.2)

2 DOSAGE AND ADMINISTRATION

- Do NOT substitute TRODELVY for or use with other drugs containing irinotecan or its active metabolite SN-38. (2.1)
- For intravenous infusion only. Do not administer as an intravenous push or bolus.
- The recommended dose is 10 mg/kg once weekly on Days 1 and 8 of continuous 21-day treatment cycles until disease progression or unacceptable toxicity. (2.2)
- Premedication for prevention of infusion reactions and prevention of chemotherapy-induced nausea and vomiting is recommended. (2.2)
- Primary prophylaxis with G-CSF is recommended starting in the first cycle in all patients at increased risk of febrile neutropenia. (2.2)
- Monitor patients during the infusion and for at least 30 minutes after completion of infusion. Treatment interruption and/or dose reduction may be needed to manage adverse reactions. (2.2)
- See Full Prescribing Information for preparation and administration instructions. (2.4)

3 DOSAGE FORMS AND STRENGTHS

For injection: 180 mg lyophilized powder in single-dose vials for reconstitution. (3)

4 CONTRAINDICATIONS

Severe hypersensitivity reaction to TRODELVY. (4, 5.3)

5 WARNINGS AND PRECAUTIONS

- Hypersensitivity and Infusion-Related Reactions: Hypersensitivity reactions including severe anaphylactic reactions have been observed. Monitor patients for infusion-related reactions. Permanently discontinue TRODELVY if severe or life-threatening reactions occur. (5.3)
- Nausea/Vomiting: Use antiemetic preventive treatment and withhold TRODELVY for patients with Grade 3 nausea or Grade 3–4 vomiting at the time of scheduled treatment. (5.4)
- Patients with Reduced UGT1A1 Activity: Individuals who are homozygous for the uridine diphosphate-glucuronosyl transferase 1A1 (UGT1A1)*28 allele are at increased risk for neutropenia, febrile neutropenia, and anemia following initiation of TRODELVY treatment. (5.5)
- Embryo-Fetal Toxicity: TRODELVY can cause fetal harm. Advise patients of potential risk to a fetus and to use effective contraception. (5.6, 8.1, 8.3)

6 ADVERSE REACTIONS

Most common adverse reactions (incidence ≥25%) are (including laboratory abnormalities) were decreased leukocyte count, decreased neutrophil count, decreased hemoglobin, diarrhea, nausea, decreased lymphocyte count, fatigue, alopecia, constipation, increased glucose, decreased albumin, vomiting, decreased appetite, decreased creatinine clearance, increased alkaline phosphatase, decreased magnesium, decreased potassium, and decreased sodium. (6.1)

To report SUSPECTED ADVERSE REACTIONS, contact Gilead Sciences, Inc. at 1-888-983-4668 or FDA at 1-800-FDA-1088 or www.fda.gov/medwatch.

7 DRUG INTERACTIONS

- UGT1A1 inhibitors or inducers: Avoid concomitant use. (7)

8 USE IN SPECIFIC POPULATIONS

- Lactation: Advise not to breastfeed. (8.2)

FULL PRESCRIBING INFORMATION

WARNING: NEUTROPENIA AND DIARRHEA

- TRODELVY can cause severe, life-threatening, or fatal neutropenia. Withhold TRODELVY for absolute neutrophil count below 1500/mm^3 or neutropenic fever. Monitor blood cell counts periodically during treatment. Primary prophylaxis with G-CSF is recommended for all patients at increased risk of febrile neutropenia [see Dosage and Administration (2.3)]. Initiate anti-infective treatment in patient with febrile neutropenia without delay [see Warnings and Precautions (5.1)].
- TRODELVY can cause severe diarrhea. Monitor patients with diarrhea and give fluid and electrolytes as needed. At the onset of diarrhea, evaluate for infectious causes and, if negative, promptly initiate loperamide [see Warnings and Precautions (5.2)]. If severe diarrhea occurs, withhold TRODELVY until resolved to ≤ Grade 1 and reduce subsequent doses [see Dosage and Administration (2.3)].

1 INDICATIONS AND USAGE

1.1 Locally Advanced or Metastatic Breast Cancer

- TRODELVY is indicated for the treatment of adult patients with unresectable locally advanced or metastatic triple-negative breast cancer (mTNBC) who have received two or more prior systemic therapies, at least one of them for metastatic disease.
- TRODELVY is indicated for the treatment of adult patients with unresectable locally advanced or metastatic hormone receptor (HR)-positive, human epidermal growth factor receptor 2 (HER2)-negative (IHC 0, IHC 1+ or IHC 2+/ISH–) breast cancer who have received endocrine-based therapy and at least two additional systemic therapies in the metastatic setting.

2 DOSAGE AND ADMINISTRATION

2.1 Important Use Information

Do NOT substitute TRODELVY for or use with other drugs containing irinotecan or its active metabolite SN-38.

2.2 Recommended Dosage

The recommended dosage of TRODELVY is 10 mg/kg administered as an intravenous infusion once weekly on Days 1 and 8 of 21-day treatment cycles. Continue treatment until disease progression or unacceptable toxicity. Do not administer TRODELVY at doses greater than 10 mg/kg.

Administer TRODELVY as an intravenous infusion only. Do not administer as an intravenous push or bolus.

First infusion: Administer infusion over 3 hours. Observe patients during the infusion and for at least 30 minutes following the initial dose, for signs or symptoms of infusion-related reactions [see Warning and Precautions (5.3)].

Subsequent infusions: Administer infusion over 1 to 2 hours if prior infusions were tolerated. Observe patients during the infusion and for at least 30 minutes after infusion.

Premedication

Prior to each dose of TRODELVY, premedication for prevention of infusion reactions and prevention of chemotherapy-induced nausea and vomiting (CINV) is recommended.

- Premedicate with antipyretics, H1 and H2 blockers prior to infusion, and corticosteroids may be used for patients who had prior infusion reactions.
- Premedicate with a two or three drug combination regimen (e.g., dexamethasone with either a 5-HT3 receptor antagonist or an NK1 receptor antagonist, as well as other drugs as indicated).

Prophylaxis for Neutropenia

Primary prophylaxis with granulocyte colony-stimulating factor (G-CSF) is recommended starting in the first cycle for all patients at increased risk of febrile neutropenia [see Warnings and Precautions (5.1)].

2.3 Dose Modifications for Adverse Reactions

Management of adverse reactions may require temporary interruption, dose reduction, or treatment discontinuation of TRODELVY as described in Tables 1 and 2. Do not re-escalate the TRODELVY dose after a dose reduction for adverse reactions has been made.

Table 1: Dosage Reduction Levels
Dose Level | Dosage and Schedule
Recommended starting dose | 10 mg/kg once weekly on Days 1 and 8 of 21-day treatment cycles
First dose reduction | Reduce to 7.5 mg/kg
Second dose reduction | Reduce to 5 mg/kg
Requirement for further dose reduction | Permanently discontinue TRODELVY

The recommended dosage modifications for adverse reactions are provided in Table 2.

Table 2: Dose Modifications for Adverse Reactions
Adverse reactions | Severity | Dose Modification
Neutropenia [see Warnings and Precautions (5.1)] | - Grade 3–4 neutropenia (Absolute Neutrophil Count [ANC] <1000/mm^3) or febrile neutropenia | - Withhold TRODELVY until ANC ≥1500/mm^3 for Day 1 dose or ANC ≥1000/mm^3 for Day 8 Dose - Administer G-CSF during treatment as clinically indicated. - Reduce one dose level for each occurrence of febrile neutropenia or prolonged Grade 3–4 neutropenia, or discontinue according to Table 1.
Nausea/Vomiting/ Diarrhea [see Warnings and Precautions (5.2, 5.4)] | - Grade 3–4 nausea, vomiting or diarrhea that is not controlled with antiemetics or anti-diarrheal agents | - Withhold TRODELVY until resolved to ≤ Grade 1 - Reduce one dose level with each occurrence, or discontinue according to Table 1.
Infusion-Related Reaction [see Warnings and Precautions (5.3)] | - Grade 1–3 infusion-related reactions | - Slow infusion rate or interrupt the infusion
Infusion-Related Reaction [see Warnings and Precautions (5.3)] | - Grade 4 infusion-related reactions | - Discontinue TRODELVY.
Other Toxicities | Other Grade 3–4 toxicities of any duration despite optimal medical management | - Withhold TRODELVY until resolved to ≤ Grade 1 - Reduce one dose level with each occurrence or discontinue according to Table 1.

2.4 Preparation and Administration

Reconstitution

- TRODELVY is a hazardous drug.
- Follow applicable special handling and disposal procedures^1.
- Calculate the required dose (mg) of TRODELVY based on the patient's current body weight [see Dosage and Administration (2.2)].
- Using a sterile syringe, slowly inject 20 mL of 0.9% Sodium Chloride Injection, USP, into each 180 mg TRODELVY vial. Each vial contains overfill to compensate for liquid loss during preparation and after reconstitution, the total resulting volume delivers a concentration of 10 mg/mL.
- Gently swirl vials and allow to dissolve for up to 15 minutes. Do not shake. Parenteral drug products should be inspected visually for particulate matter and discoloration prior to administration, whenever solution and container permit. The solution should be free of visible particulates, clear and yellow. Do not use the reconstituted solution if it is cloudy or discolored.
- Use immediately to prepare a diluted TRODELVY infusion solution.

Dilution

- Calculate the required amount of the reconstituted TRODELVY solution needed to obtain the appropriate dose according to the patient's body weight.
- Determine the final volume of the infusion solution to deliver the appropriate dose at a TRODELVY concentration range of 1.1 mg/mL to 3.4 mg/mL.
- Use 0.9% Sodium Chloride Injection, USP only since the stability of the reconstituted TRODELVY solution has not been determined with other infusion-based solutions. Use a polyvinyl chloride, polypropylene/polyethylene, polyolefin, or ethylene vinyl acetate infusion bag.
- Withdraw and discard the volume of 0.9% Sodium Chloride Injection, USP from the final infusion bag that is necessary to achieve the indicated TRODELVY concentration following the addition of the calculated amount of reconstituted TRODELVY solution.
- Withdraw the calculated amount of the reconstituted TRODELVY solution from the vial(s) using a syringe. Discard any unused portion remaining in the vial(s).
- To minimize foaming, slowly inject the calculated amount of reconstituted TRODELVY solution into the infusion bag. Do not shake the contents.
- If not used immediately, the infusion bag containing TRODELVY solution can be stored refrigerated at 2°C to 8°C (36°F to 46°F) for up to 24 hours protected from light. After refrigeration, administer diluted solution at room temperature up to 25°C (77°F) within 8 hours (including infusion time).

Do Not Freeze or Shake.

Administration

- Administer TRODELVY as an intravenous infusion. Protect infusion bag from light. The infusion bag should be covered during administration to the patient until dosing is complete. It is not necessary to cover the infusion tubing or to use light-protective tubing during the infusion.
- An infusion pump may be used.
- Do not mix TRODELVY, or administer as an infusion, with other medicinal products.
- Upon completion of the infusion, flush the intravenous line with 20 mL 0.9% Sodium Chloride Injection, USP.

3 DOSAGE FORMS AND STRENGTHS

For injection: 180 mg off-white to yellowish lyophilized powder in a single-dose vial.

4 CONTRAINDICATIONS

TRODELVY is contraindicated in patients who have experienced a severe hypersensitivity reaction to TRODELVY [see Warnings and Precautions (5.3)].

5 WARNINGS AND PRECAUTIONS

5.1 Neutropenia

TRODELVY can cause severe, life-threatening, or fatal neutropenia as early as the first cycle of treatment. Neutropenia occurred in 64% of patients treated with TRODELVY. Grade 3–4 neutropenia occurred in 49% of patients. Febrile neutropenia occurred in 6% of patients. The median time to first onset of neutropenia (including febrile neutropenia) was 16 days (range: 1 to 435 days). Neutropenia occurred earlier in patients with reduced UGT1A1 activity [see Warnings and Precautions (5.5)]. Neutropenic colitis occurred in 1.4% of patients.

Primary prophylaxis with G-CSF is recommended starting in the first cycle of treatment in all patients at increased risk of febrile neutropenia, including older patients, patients with previous neutropenia, poor performance status, organ dysfunction, or multiple comorbidities.

Monitor absolute neutrophil count (ANC) during treatment. Withhold TRODELVY for ANC below 1500/mm^3 on Day 1 of any cycle or below 1000/mm^3 on Day 8 of any cycle. Withhold TRODELVY for neutropenic fever. Dose modifications may be required due to neutropenia. Treat neutropenia with G-CSF and administer prophylaxis in subsequent cycles as clinically indicated or indicated in Table 2 [see Dosage and Administration (2.3)].

5.2 Diarrhea

TRODELVY can cause severe diarrhea. Diarrhea occurred in 64% of all patients treated with TRODELVY. Grade 3–4 diarrhea occurred in 11% of all patients treated with TRODELVY. One patient had intestinal perforation following diarrhea. Diarrhea that led to dehydration and subsequent acute kidney injury occurred in 0.7% of all patients.

Withhold TRODELVY for Grade 3–4 diarrhea at the time of scheduled treatment administration and resume when resolved to ≤ Grade 1 [see Dosage and Administration (2.3)].

At the onset of diarrhea, evaluate for infectious causes and if negative, promptly initiate loperamide, 4 mg initially followed by 2 mg with every episode of diarrhea for a maximum of 16 mg daily. Discontinue loperamide 12 hours after diarrhea resolves. Additional supportive measures (e.g., fluid and electrolyte substitution) may also be employed as clinically indicated.

Patients who exhibit an excessive cholinergic response to treatment with TRODELVY (e.g., abdominal cramping, diarrhea, salivation, etc.) can receive appropriate premedication (e.g., atropine) for subsequent treatments.

5.3 Hypersensitivity and Infusion-Related Reactions

TRODELVY can cause serious hypersensitivity reactions including life-threatening anaphylactic reactions. Severe signs and symptoms included cardiac arrest, hypotension, wheezing, angioedema, swelling, pneumonitis, and skin reactions [see Contraindications (4)].

Hypersensitivity reactions within 24 hours of dosing occurred in 35% of patients treated with TRODELVY. Grade 3–4 hypersensitivity occurred in 2% of patients treated with TRODELVY. The incidence of hypersensitivity reactions leading to permanent discontinuation of TRODELVY was 0.2%. The incidence of anaphylactic reactions was 0.2%.

Premedication for infusion reactions in patients receiving TRODELVY is recommended. Have medications and emergency equipment to treat infusion-related reactions, including anaphylaxis, available for immediate use when administering TRODELVY [see Dosage and Administration (2.2)].

Closely monitor patients for hypersensitivity and infusion-related reactions during each TRODELVY infusion and for at least 30 minutes after completion of each infusion [see Dosage and Administration (2.3)].

Permanently discontinue TRODELVY for Grade 4 infusion-related reactions [see Dosage and Administration (2.3)].

5.4 Nausea and Vomiting

TRODELVY is emetogenic and can cause severe nausea and vomiting. Nausea occurred in 64% of all patients treated with TRODELVY. Grade 3–4 nausea occurred in 3% of patients.

Vomiting occurred in 35% of all patients treated with TRODELVY. Grade 3–4 vomiting occurred in 2% of these patients.

Premedicate with a two or three drug combination regimen (e.g., dexamethasone with either a 5-HT3 receptor antagonist or an NK1 receptor antagonist as well as other drugs as indicated) for prevention of chemotherapy-induced nausea and vomiting (CINV) [see Dosage and Administration (2.2)].

Withhold TRODELVY doses for Grade 3 nausea or Grade 3–4 vomiting at the time of scheduled treatment administration and resume with additional supportive measures when resolved to ≤ Grade 1 [see Dosage and Administration (2.3)].

Additional antiemetics and other supportive measures may also be employed as clinically indicated. All patients should be given take-home medications with clear instructions for prevention and treatment of nausea and vomiting.

5.5 Increased Risk of Adverse Reactions in Patients with Reduced UGT1A1 Activity

Patients homozygous for the uridine diphosphate-glucuronosyl transferase 1A1 (UGT1A1)*28 allele are at increased risk for neutropenia, febrile neutropenia, and anemia; and may be at increased risk for other adverse reactions when treated with TRODELVY.

The incidence of neutropenia and anemia was analyzed in 948 patients who received TRODELVY and had UGT1A1 genotype results. In patients homozygous for the UGT1A1 *28 allele (n=112), the incidence of Grade 3–4 neutropenia was 58%. In patients heterozygous for the UGT1A1*28 allele (n=420), the incidence of Grade 3–4 neutropenia was 49%. In patients homozygous for the wild-type allele (n=416), the incidence of Grade 3–4 neutropenia was 43% [see Clinical Pharmacology (12.5)]. In patients homozygous for the UGT1A1 *28 allele, the incidence of Grade 3–4 anemia was 21%. In patients heterozygous for the UGT1A1*28 allele, the incidence of Grade 3–4 anemia was 10%. In patients homozygous for the wild-type allele, the incidence of Grade 3–4 anemia was 9%.

The median time to first neutropenia including febrile neutropenia was 9 days in patients homozygous for the UGT1A1*28 allele, 15 days in patients heterozygous for the UGT1A1*28 allele, and 20 days in patients homozygous for the wild-type allele. The median time to first anemia was 21 days in patients homozygous for the UGT1A1*28 allele, 25 days in patients heterozygous for the UGT1A1*28 allele, and 28 days in patients homozygous for the wild-type allele.

Closely monitor patients with known reduced UGT1A1 activity for adverse reactions. Withhold or permanently discontinue TRODELVY based on clinical assessment of the onset, duration and severity of the observed adverse reactions in patients with evidence of acute early-onset or unusually severe adverse reactions, which may indicate reduced UGT1A1 enzyme activity [see Dosage and Administration (2.3)].

5.6 Embryo-Fetal Toxicity

Based on its mechanism of action, TRODELVY can cause teratogenicity and/or embryo-fetal lethality when administered to a pregnant woman. TRODELVY contains a genotoxic component, SN-38, and targets rapidly dividing cells [see Clinical Pharmacology (12.1) and Nonclinical Toxicology (13.1)]. Advise pregnant women and females of reproductive potential of the potential risk to a fetus. Advise females of reproductive potential to use effective contraception during treatment with TRODELVY and for 6 months after the last dose. Advise male patients with female partners of reproductive potential to use effective contraception during treatment with TRODELVY and for 3 months after the last dose [see Use in Specific Populations (8.1, 8.3)].

6 ADVERSE REACTIONS

The following adverse reactions are discussed in greater detail in other sections of the label:

- Neutropenia [see Warnings and Precautions (5.1)]
- Diarrhea [see Warnings and Precautions (5.2)]
- Hypersensitivity and Infusion-Related Reactions [see Warnings and Precautions (5.3)]
- Nausea and Vomiting [see Warnings and Precautions (5.4)]

6.1 Clinical Trials Experience

Because clinical trials are conducted under widely varying conditions, adverse reaction rates observed in the clinical trials of a drug cannot be directly compared to rates in the clinical trials of another drug and may not reflect the rates observed in clinical practice.

The pooled safety population described in the Warnings and Precautions section reflect exposure to TRODELVY in 1063 patients, which included 366 patients with mTNBC and 322 patients with hormone receptor-positive (HR+)/human epidermal growth factor receptor 2-negative (HER2-) breast cancer from IMMU-132-01, ASCENT, and TROPiCS-02; and 375 patients with other tumor types. TRODELVY was administered as an intravenous infusion once weekly on Days 1 and 8 of 21-day treatment cycles at doses of 10 mg/kg until disease progression or unacceptable toxicity. Among the 1063 patients treated with TRODELVY, the median duration of treatment was 4.1 months (range: 0 to 63 months). In this pooled safety population, the most common (≥ 25%) adverse reactions including laboratory abnormalities were decreased leukocyte count (84%), decreased neutrophil count (75%), decreased hemoglobin (69%), diarrhea (64%), nausea (64%), decreased lymphocyte count (63%), fatigue (51%), alopecia (45%), constipation (37%), increased glucose (37%), decreased albumin (35%), vomiting (35%), decreased appetite (30%), decreased creatinine clearance (28%), increased alkaline phosphatase (28%), decreased magnesium (27%), decreased potassium (26%), and decreased sodium (26%).

Locally Advanced or Metastatic Triple-Negative Breast Cancer

ASCENT Study

The safety of TRODELVY was evaluated in a randomized, active-controlled, open-label study (ASCENT) in patients with mTNBC who had previously received a taxane and at least two prior chemotherapies. Patients were randomized (1:1) to receive either TRODELVY (n=258) or single agent chemotherapy (n=224) and were treated until disease progression or unacceptable toxicity [see Clinical Studies (14.1)]. For patients treated with TRODELVY, the median duration of treatment was 4.4 months (range: 0 to 23 months).

Serious adverse reactions occurred in 27% of patients receiving TRODELVY. Serious adverse reactions in > 1% of patients receiving TRODELVY included neutropenia (7%), diarrhea (4%), and pneumonia (3%). Fatal adverse reactions occurred in 1.2% of patients who received TRODELVY, including respiratory failure (0.8%) and pneumonia (0.4%). TRODELVY was permanently discontinued for adverse reactions in 5% of patients. Adverse reactions leading to permanent discontinuation in ≥ 1 % of patients who received TRODELVY were pneumonia (1%) and fatigue (1%).

Adverse reactions leading to a treatment interruption of TRODELVY occurred in 63% of patients. The most frequent (≥5%) adverse reactions leading to a treatment interruption were neutropenia (47%), diarrhea (5%), respiratory infection (5%), and leukopenia (5%).

Adverse reactions leading to a dose reduction of TRODELVY occurred in 22% of patients. The most frequent (>4%) adverse reactions leading to a dose reduction were neutropenia (11%) and diarrhea (5%).

Granulocyte-colony stimulating factor (G-CSF) was used in 44% of patients who received TRODELVY.

Tables 3 and 4 summarize adverse reactions and laboratory abnormalities, respectively, in the ASCENT study.

Table 3: Adverse Reactions in ≥ 10% of Patients with mTNBC in ASCENT
 | TRODELVY (n=258) |  | Single Agent Chemotherapy (n=224)
Adverse Reaction | All Grades % | Grade 3 – 4 % | All Grades % | Grade 3 – 4 %
Gastrointestinal disorders
Diarrhea | 59 | 11 | 17 | 1
Nausea | 57 | 3 | 26 | 0.4
Vomiting | 33 | 2 | 16 | 1
Constipation | 37 | 0.4 | 23 | 0
Abdominal Pain | 30 | 3 | 12 | 1
Stomatitis [Including stomatitis, glossitis, mouth ulceration, and mucosal inflammation] | 17 | 2 | 13 | 1
General disorders and administration site conditions
Fatigue [Including fatigue and asthenia] | 65 | 6 | 50 | 9
Pyrexia | 15 | 0.4 | 14 | 2
Infections and infestation
Urinary tract infection | 13 | 0.4 | 8 | 0.4
Upper respiratory tract infection | 12 | 0 | 3 | 0
Metabolism and nutrition disorders
Decreased appetite | 28 | 2 | 21 | 1
Musculoskeletal and connective tissue disorders
Back pain | 16 | 1 | 14 | 2
Arthralgia | 12 | 0.4 | 7 | 0
Nervous system disorders
Headache | 18 | 0.8 | 13 | 0.4
Dizziness | 10 | 0 | 7 | 0
Psychiatric disorders
Insomnia | 11 | 0 | 5 | 0
Respiratory, thoracic and mediastinal disorders
Cough | 24 | 0 | 18 | 0.4
Skin and subcutaneous tissue disorders
Alopecia | 47 | 0 | 16 | 0
Rash | 12 | 0.4 | 5 | 0.4
Pruritus | 10 | 0 | 3 | 0
*Single agent chemotherapy included one of the following single-agents: eribulin (n=139), capecitabine (n=33), gemcitabine (n=38), or vinorelbine (except if patient had ≥ Grade 2 neuropathy, n=52).
Graded per NCI CTCAE v.5.0.

Table 4: Laboratory Abnormalities in > 10% of Patients with mTNBC in ASCENT
Laboratory Abnormality | TRODELVY (n=258) |  | Single Agent Chemotherapy (n=224)
 | All Grades (%) | Grade 3 – 4 (%) | All Grades (%) | Grade 3 – 4 (%)
Hematology
Decreased hemoglobin | 94 | 9 | 57 | 6
Decreased lymphocyte count | 88 | 31 | 40 | 24
Decreased leukocyte count | 86 | 41 | 53 | 25
Decreased neutrophil count | 78 | 49 | 48 | 36
Decreased platelet count | 23 | 1.2 | 25 | 2.7
Chemistry
Increased glucose | 49 | 2.3 | 43 | 2.8
Decreased calcium | 36 | 1.6 | 21 | 1.4
Decreased magnesium | 33 | 0.4 | 20 | 0
Decreased potassium | 33 | 4.3 | 28 | 0.9
Increased albumin | 32 | 0.8 | 25 | 1.4
Increased aspartate aminotransferase | 27 | 1.2 | 32 | 1.4
Increased alanine aminotransferase | 26 | 1.2 | 26 | 1.8
Increased alkaline phosphatase | 26 | 0 | 17 | 0.5
Decreased phosphate | 26 | 7.8 | 20 | 3.3
Decreased sodium | 22 | 0.4 | 17 | 0.5
Increased lactate dehydrogenase | 18 | 0 | 22 | 0
Decreased glucose | 10 | 0 | 3.2 | 0

Study IMMU-132-01

The safety of TRODELVY was evaluated in a single-arm, open-label study (IMMU-132-01) in patients with mTNBC and other malignancies, which included 108 patients with mTNBC who had received at least two prior anticancer therapies for metastatic disease [see Clinical Studies (14.1)]. TRODELVY was administered as an intravenous infusion once weekly on Days 1 and 8 of 21-day treatment cycles at doses up to 10 mg/kg until disease progression or unacceptable toxicity. The median treatment duration in these 108 patients was 5.1 months (range: 0 to 51 months).

Serious adverse reactions occurred in 31% of the patients. Serious adverse reactions in > 1% of patients receiving TRODELVY included febrile neutropenia (6%) vomiting (5%), nausea (3%), dyspnea (3%), diarrhea (4%), anemia (2%), pleural effusion, neutropenia, pneumonia, dehydration (each 2%).

TRODELVY was permanently discontinued for adverse reactions in 2% of patients. Adverse reactions leading to permanent discontinuation were anaphylaxis, anorexia/fatigue, headache (each 0.9%). Forty- five percent (45%) of patients experienced an adverse reaction leading to treatment interruption. The most common adverse reaction leading to treatment interruption was neutropenia (33%). Adverse reactions leading to dose reduction occurred in 33% of patients treated with TRODELVY, with 24% having one dose reduction, and 9% with two dose reductions. The most common adverse reaction leading to dose reductions was neutropenia/febrile neutropenia.

Tables 5 and 6 summarize adverse reactions and laboratory abnormalities occurring in ≥ 10% of patients with mTNBC in the IMMU-132-01 study.

Table 5: Adverse Reactions in ≥ 10% of Patients with mTNBC in IMMU-132-01
Adverse Reaction | TRODELVY (n=108)
Adverse Reaction | Grade 1–4 (%) | Grade 3–4 (%)
Any adverse reaction | 100 | 71
Gastrointestinal disorders | 95 | 21
Nausea | 69 | 6
Diarrhea | 63 | 9
Vomiting | 49 | 6
Constipation | 34 | 1
Abdominal pain [Including abdominal pain, distention, pain (upper), discomfort, tenderness.] | 26 | 1
Mucositis [Including stomatitis, esophagitis, and mucosal inflammation] | 14 | 1
General disorders and administration site conditions | 77 | 9
Fatigue [Including fatigue and asthenia.] | 57 | 8
Edema [Including edema; and peripheral, localized, and periorbital edema] | 19 | 0
Pyrexia | 14 | 0
Metabolism and nutrition disorders | 68 | 22
Decreased appetite | 30 | 1
Dehydration | 13 | 5
Skin and subcutaneous tissue disorders | 63 | 4
Alopecia | 38 | 0
Rash [Including rash; maculopapular, erythematous, generalized rash; dermatitis acneiform; skin disorder, irritation, and exfoliation] | 31 | 3
Pruritus | 17 | 0
Dry Skin | 15 | 0
Nervous system disorders | 56 | 4
Headache | 23 | 1
Dizziness | 22 | 0
Neuropathy [Including gait disturbance, hypoesthesia, muscular weakness, paresthesia, peripheral and sensory neuropathy] | 24 | 0
Dysgeusia | 11 | 0
Infections and infestations | 55 | 12
Urinary Tract Infection | 21 | 3
Respiratory Infection [Including lower and upper respiratory tract infection, pneumonia, influenza, viral upper respiratory infection, bronchitis and respiratory syncytial virus infection] | 26 | 3
Musculoskeletal and connective tissue disorders | 54 | 1
Back pain | 23 | 0
Arthralgia | 17 | 0
Pain in extremity | 11 | 0
Respiratory, thoracic and mediastinal disorders | 54 | 5
Cough [Includes cough and productive cough] | 22 | 0
Dyspnea [Includes dyspnea and exertional dyspnea] | 21 | 3
Psychiatric disorders | 26 | 1
Insomnia | 13 | 0
Graded per NCI CTCAE v. 4.0

Table 6: Laboratory Abnormalities observed in ≥ 10% of Patients while receiving TRODELVY in IMMU-132-01
Laboratory Abnormality | TRODELVY (n=108)
Laboratory Abnormality | All Grades (%) | Grade 3–4 (%)
Hematology
Decreased hemoglobin | 93 | 6
Decreased leukocyte count | 91 | 26
Decreased neutrophil count | 82 | 32
Increased activated partial thromboplastin time | 60 | 12
Decreased platelet count | 30 | 3
Chemistry
Increased alkaline phosphatase | 57 | 2
Decreased magnesium | 51 | 3
Decreased calcium | 49 | 3
Increased aspartate aminotransferase | 45 | 3
Decreased albumin | 39 | 1
Increased alanine aminotransferase | 35 | 2
Increased glucose | 31 | 2.8
Decreased phosphate | 29 | 5
Decrease magnesium | 27 | 1.9
Decreased phosphate | 27 | 6.5
Decreased sodium | 25 | 4.7
Decreased potassium | 24 | 3.7
Decreased glucose | 19 | 2

Locally Advanced or Metastatic HR-Positive, HER2-Negative Breast Cancer

TROPiCS-02 Study

The safety of TRODELVY was evaluated in a randomized, active-controlled, open-label, study (TROPiCS-02) in patients with unresectable locally advanced or metastatic HR-positive, HER2-negative breast cancer whose disease has progressed after the following in any setting: a CDK 4/6 inhibitor, endocrine therapy, and a taxane; patients received at least two prior chemotherapies in the metastatic setting (one of which could be in the neoadjuvant or adjuvant setting if progression occurred within 12 months). Patients were randomized (1:1) to receive either TRODELVY (n=268) or single agent chemotherapy (n=249) and were treated until disease progression or unacceptable toxicity [see Clinical Studies (14.2)]. For patients treated with TRODELVY, the median duration of treatment was 4.1 months (range: 0 to 63 months).

Serious adverse reactions occurred in 28% of patients receiving TRODELVY. Serious adverse reactions in > 1% of patients receiving TRODELVY included diarrhea (5%), febrile neutropenia (4%), neutropenia (3%), abdominal pain, colitis, neutropenic colitis, pneumonia, and vomiting (each 2%). Fatal adverse reactions occurred in 2% of patients who received TRODELVY including arrhythmia, COVID-19, nervous system disorder, pulmonary embolism, and septic shock (each 0.4%). TRODELVY was permanently discontinued for adverse reactions in 6% of patients. The most frequent (≥ 0.5%) adverse reactions leading to permanent discontinuation in patients who received TRODELVY were asthenia, general physical health deterioration, and neutropenia (each 0.7%).

Adverse reactions leading to a treatment interruptions of TRODELVY occurred in 66% of patients. The most frequent (≥ 5%) adverse reaction leading to treatment interruption was neutropenia (50%).

Adverse reaction leading to a dose reduction of TRODELVY occurred in 33% of patients. The most frequent (> 5%) adverse reaction leading to dose reduction were neutropenia (16%) and diarrhea (8%). G-CSF was used in 54% of patients who received TRODELVY.

Tables 7 and 8 summarize adverse reactions and laboratory abnormalities in the TROPiCS-02 study.

Table 7: Adverse Reactions in ≥ 10% of Patients with HR+/HER2- mBC in TROPiCS-02
 | TRODELVY (n=268) |  | Single Agent Chemotherapy (n=249)
Adverse Reaction | All Grades % | Grade 3 – 4 % | All Grades % | Grade 3 – 4 %
Gastrointestinal disorders
Diarrhea | 62 | 10 | 23 | 1
Nausea | 59 | 1 | 35 | 3
Constipation | 34 | 1 | 25 | 0
Vomiting | 23 | 1 | 16 | 2
Abdominal Pain | 20 | 0 | 14 | 0
Dyspepsia [Including dyspepsia, gastroesophageal reflux disease.] | 11 | 0 | 6 | 0
General disorders and administration site conditions
Fatigue [Including fatigue, asthenia.] | 60 | 8 | 51 | 4
Metabolism and nutrition disorders
Decreased appetite | 21 | 2 | 21 | 0
Hypokalemia | 10 | 2 | 4 | 0
Musculoskeletal and connective tissue disorders
Arthralgia | 15 | 0 | 12 | 0
Nervous system disorders
Headache | 16 | 1 | 15 | 1
Respiratory, thoracic and mediastinal disorders
Dyspnea [Including dyspnea; exertional dyspnea] | 20 | 0 | 17 | 0
Cough | 12 | 0 | 7 | 0
Skin and subcutaneous tissue disorders
Alopecia | 48 | 0 | 19 | 0
Pruritus | 12 | 0 | 2 | 0
*Single agent chemotherapy included one of the following single-agents: eribulin (n=130), vinorelbine (n=63), gemcitabine (n=56), or capecitabine (n=22).
Graded per NCI CTCAE v.5.0.

Other clinically significant adverse reactions in TROPiCS-02 (≤ 10%) include: hypotension (5%), pain (5%), rhinorrhea (5%), hypocalcemia (3%), nasal congestion (3%), skin hyperpigmentation, (3%), colitis or neutropenic colitis (2%), hyponatremia (2%), pneumonia (2%), proteinuria (1%), enteritis (0.4%).

Table 8: Laboratory Abnormalities in > 10% of Patients with HR+/HER2- mBC in TROPiCS-02
Laboratory Abnormality | TRODELVY (n=268) |  | Single Agent Chemotherapy (n=249)
 | All Grades (%) | Grade 3 – 4 (%) | All Grades (%) | Grade 3 – 4 (%)
Hematology
Decreased leukocyte count | 88 | 38 | 73 | 26
Decreased neutrophil count | 83 | 53 | 67 | 40
Decreased hemoglobin | 73 | 8 | 59 | 5
Decreased lymphocyte count | 65 | 21 | 47 | 14
Decreased platelet count | 21 | 1 | 30 | 4
Eosinophilia | 13 | 0 | 4 | 0
Chemistry
Increased glucose | 37 | 0 | 31 | 0
Decreased albumin | 32 | 0 | 27 | 0.4
Decreased creatinine clearance | 24 | 2 | 19 | 1
Increased alkaline phosphatase | 23 | 0 | 23 | 1
Decreased potassium | 22 | 3 | 12 | 0.4
Increased alanine aminotransferase | 21 | 1 | 31 | 2
Decreased sodium | 19 | 1 | 17 | 0.4
Decreased magnesium | 18 | 0 | 15 | 0
Decreased phosphate | 17 | 0 | 10 | 0
Increased phosphate | 16 | 0 | 16 | 0
Increased lactate dehydrogenase | 16 | 0 | 28 | 0
Increased aspartate aminotransferase | 15 | 2 | 25 | 1
Increased potassium | 14 | 2 | 9 | 0

7 DRUG INTERACTIONS

7.1 Effect of Other Drugs on TRODELVY

UGT1A1 Inhibitors

Concomitant administration of TRODELVY with inhibitors of UGT1A1 may increase the incidence of adverse reactions due to potential increase in systemic exposure to SN-38 [see Warning and Precaution (5.5) and Clinical Pharmacology (12.3, 12.5)]. Avoid administering UGT1A1 inhibitors with TRODELVY.

UGT1A1 Inducers

Exposure to SN-38 may be reduced in patients concomitantly receiving UGT1A1 enzyme inducers [see Warning and Precaution (5.5) and Clinical Pharmacology (12.3, 12.5)]. Avoid administering UGT1A1 inducers with TRODELVY.

8 USE IN SPECIFIC POPULATIONS

8.1 Pregnancy

Risk Summary

Based on its mechanism of action, TRODELVY can cause teratogenicity and/or embryo-fetal lethality when administered to a pregnant woman. There are no available data in pregnant women to inform the drug-associated risk. TRODELVY contains a genotoxic component, SN-38, and is toxic to rapidly dividing cells [see Clinical Pharmacology (12.1) and Nonclinical Toxicology (13.1)]. Advise pregnant women and females of reproductive potential of the potential risk to a fetus.

The estimated background risk of major birth defects and miscarriage for the indicated population is unknown. In the U.S. general population, the estimated background risk of major birth defects and miscarriage in clinically recognized pregnancies is 2 – 4% and 15 – 20%, respectively.

Data

Animal data

There were no reproductive and developmental toxicology studies conducted with sacituzumab govitecan-hziy.

8.2 Lactation

Risk Summary

There is no information regarding the presence of sacituzumab govitecan-hziy or SN-38 in human milk, the effects on the breastfed child, or the effects on milk production. Because of the potential for serious adverse reactions in a breastfed child, advise women not to breastfeed during treatment and for 1 month after the last dose of TRODELVY.

8.3 Females and Males of Reproductive Potential

Pregnancy Testing

Verify the pregnancy status of females of reproductive potential prior to the initiation of TRODELVY.

Contraception

Females

TRODELVY can cause fetal harm when administered to a pregnant woman [see Use in Specific Populations (8.1)]. Advise females of reproductive potential to use effective contraception during treatment with TRODELVY and for 6 months after the last dose.

Males

Because of the potential for genotoxicity, advise male patients with female partners of reproductive potential to use effective contraception during treatment with TRODELVY and for 3 months after the last dose.

Infertility

Females

Based on findings in animals, TRODELVY may impair fertility in females of reproductive potential [see Nonclinical Toxicology (13.1)].

8.4 Pediatric Use

Safety and effectiveness of TRODELVY have not been established in pediatric patients.

8.5 Geriatric Use

Of the 366 patients with TNBC who were treated with TRODELVY, 19% of patients were 65 years and 3% were 75 years and older. Patients 65 and older had an increased incidence of neutropenia, including fatal outcomes. No other differences in safety and effectiveness were observed between patients ≥ 65 years of age and younger patients.

Of the 322 patients with HR+/HER2- breast cancer who were treated with TRODELVY, 26% of patients were 65 years and older and 6% were 75 years and older. No overall differences in effectiveness were observed between patients ≥ 65 years of age and younger patients. There was a higher discontinuation rate due to adverse reactions in patients aged 65 years or older (14%) compared with younger patients (3%).

8.6 Hepatic Impairment

No adjustment to the starting dosage is required when administering TRODELVY to patients with mild hepatic impairment [see Clinical Pharmacology (12.3)].

The safety of TRODELVY in patients with moderate (total bilirubin > 1.5 to 3.0 × ULN) or severe (total bilirubin > 3.0 × upper limit of normal [ULN]) hepatic impairment has not been established. TRODELVY has not been tested in patients with AST or ALT > 3 ULN without liver metastases, or AST or ALT > 5 ULN with liver metastases. No recommendations can be made for the starting dosage in these patients.

10 OVERDOSAGE

In a clinical trial, planned doses of up to 18 mg/kg (approximately 1.8 times the maximum recommended dose of 10 mg/kg) of TRODELVY were administered. In these patients, a higher incidence of severe neutropenia was observed.

11 DESCRIPTION

Sacituzumab govitecan-hziy is a Trop-2 directed antibody and topoisomerase inhibitor conjugate, composed of the following three components:

- the humanized monoclonal antibody, hRS7 IgG1κ (also called sacituzumab), which binds to Trop-2 (the trophoblast cell-surface antigen-2);
- the drug SN-38, a topoisomerase inhibitor;
- a hydrolysable linker (called CL2A), which links the humanized monoclonal antibody to SN-38.

The recombinant monoclonal antibody is produced by mammalian (murine myeloma) cells, while the small molecule components SN-38 and CL2A are produced by chemical synthesis. Sacituzumab govitecan-hziy contains on average 7 to 8 molecules of SN-38 per antibody molecule. Sacituzumab govitecan-hziy has a molecular weight of approximately 160 kilodaltons. Sacituzumab govitecan-hziy has the following chemical structure.

TRODELVY (sacituzumab govitecan-hziy) for injection is a sterile, preservative-free, off-white to yellowish lyophilized powder for intravenous use in a 50 mL clear glass single-dose vial, with a rubber stopper and crimp-sealed with an aluminum flip-off cap.

Each single-dose vial of TRODELVY delivers 180 mg sacituzumab govitecan-hziy, 71.7 mg 2-(N-morpholino) ethane sulfonic acid (MES), 1.8 mg polysorbate 80 and 153.99 mg trehalose. Reconstitution with 20 mL of 0.9% Sodium Chloride Injection, USP, results in a concentration of 10 mg/mL with a pH of 6.5.

12 CLINICAL PHARMACOLOGY

12.1 Mechanism of Action

Sacituzumab govitecan-hziy is a Trop-2-directed antibody-drug conjugate. Sacituzumab is a humanized antibody that recognizes Trop-2. The small molecule, SN-38, is a topoisomerase I inhibitor, which is covalently attached to the antibody by a linker. Pharmacology data suggest that sacituzumab govitecan-hziy binds to Trop-2-expressing cancer cells and is internalized with the subsequent release of SN-38 via hydrolysis of the linker. SN-38 interacts with topoisomerase I and prevents re-ligation of topoisomerase I-induced single strand breaks. The resulting DNA damage leads to apoptosis and cell death. Sacituzumab govitecan-hziy decreased tumor growth in mouse xenograft models of triple-negative breast cancer.

12.2 Pharmacodynamics

The TRODELVY exposure-response relationships and pharmacodynamic time course for efficacy have not been fully characterized.

Cardiac electrophysiology

The maximum mean change from baseline was 9.7 msec (the upper bound of the two-sided 90% confidence interval is 16.8 msec) at the recommended dose. A positive exposure-response relationship was observed between QTc increases and SN-38 concentrations.

12.3 Pharmacokinetics

The serum pharmacokinetics of sacituzumab govitecan-hziy and SN-38 were evaluated in patients with mBC who received sacituzumab govitecan-hziy as a single agent at a dose of 10 mg/kg. The pharmacokinetic parameters of sacituzumab govitecan-hziy and free SN-38 are presented in Table 9.

Table 9: Summary of Mean PK Parameters (CV%) of Sacituzumab Govitecan-hziy and Free SN-38 [Parameters estimated based on population PK analyses]
 | Sacituzumab govitecan-hziy (N=693) | Free SN-38 (N=681)
Cmax [ng/mL] | 239000 (11%) | 98.0 (45%)
AUC0–168 [ng*h/mL] | 5640000 (22%) | 3696 (56%)
Cmax: maximum serum concentration from 0–168 hours after the first dose
AUC0–168: area under serum concentration curve through 168 hours after the first dose

Distribution

Based on population pharmacokinetic analysis, steady state volume of distribution of sacituzumab govetican-hziy is 3.6L.

Elimination

The median elimination half-life (t1/2) of sacituzumab govitecan-hziy and free SN-38 in patients with metastatic triple negative breast cancer was 23.4 and 17.6 hours, respectively. Based on population pharmacokinetic analysis, the estimated mean (%CV) clearance of the sacituzumab govitecan-hziy is 0.13 L/h (12%).

Metabolism

No metabolism studies with sacituzumab govitecan-hziy have been conducted. SN-38 (the small molecule moiety of sacituzumab govitecan-hziy) is metabolized via UGT1A1. The glucuronide metabolite of SN-38 (SN-38G) was detectable in the serum of patients.

Specific Populations

Pharmacokinetic analyses in patients treated with TRODELVY did not identify an effect of age (27 to 88 years), race (White, Black, or Asian), or mild renal impairment to moderate renal impairment (CLcr 30 to 89 mL/min) on the pharmacokinetics of sacituzumab govitecan-hziy. Renal elimination is known to contribute minimally to the excretion of SN-38, the small molecule moiety of sacituzumab govitecan-hziy. There are no data on the pharmacokinetics of sacituzumab govitecan-hziy in patients with severe renal impairment (CLcr 15 to 29 mL/min), or end-stage renal disease (CLcr < 15 mL/min).

Patients with Hepatic Impairment

The exposure of sacituzumab govitecan-hziy is similar in patients with mild hepatic impairment (total bilirubin ≤ ULN with AST > ULN, or bilirubin >1.0 to ≤ 1.5 ULN with any AST; n=257) to patients with normal hepatic function (total bilirubin and AST < ULN; n=526).

Sacituzumab govitecan-hziy and free SN-38 exposures are unknown in patients with moderate (total bilirubin > 1.5 to 3.0 × ULN) or severe (total bilirubin > 3.0 × ULN) hepatic impairment.

Drug Interaction Studies

No drug-drug interaction studies were conducted with sacituzumab govitecan-hziy or its components. Inhibitors or inducers of UGT1A1 may increase or decrease SN-38 exposure, respectively [see Drug Interactions (7)].

12.5 Pharmacogenomics

SN-38 is metabolized via UGT1A1 [see Clinical Pharmacology (12.3)]. Genetic variants of the UGT1A1 gene such as the UGT1A1*28 allele lead to reduced UGT1A1 enzyme activity. Individuals who are homozygous or heterozygous for the UGT1A1*28 allele are at increased risk for neutropenia, febrile neutropenia, and anemia from TRODELVY compared to individuals who are wildtype (*1/*1) [see Warnings and Precautions (5.5)]. Approximately 20% of the Black or African American population, 10% of the White population, and 2% of the East Asian population are homozygous for the UGT1A1*28 allele (*28/*28). Approximately 40% of the Black or African American population, 50% of the White population, and 25% of the East Asian population are heterozygous for the UGT1A1*28 allele (*1/*28). Decreased function alleles other than UGT1A1*28 may be present in certain populations.

12.6 Immunogenicity

The detection of antibody formation is highly dependent on the sensitivity and specificity of the assay. Differences in assay methods preclude meaningful comparisons of the incidence of anti-drug antibodies in the studies described below with the incidence of anti-drug antibodies in other studies, including those of TRODELVY.

During the median 4-month treatment period across clinical studies in patients treated with TRODELVY, 9 (1.1%) of 785 patients developed antibodies to sacituzumab govitecan; 6 of these patients (0.8% of all patients treated with TRODELVY) had neutralizing antibodies against sacituzumab govitecan. Because of the low occurrence of anti-drug antibodies, the effect of these antibodies on the pharmacokinetics, pharmacodynamics, safety, and/or effectiveness of sacituzumab govitecan is unknown.

13 NONCLINICAL TOXICOLOGY

13.1 Carcinogenesis, Mutagenesis, Impairment of Fertility

Carcinogenicity studies have not been conducted with sacituzumab govitecan-hziy.

SN-38 was clastogenic in an in vitro mammalian cell micronucleus test in Chinese hamster ovary cells and was not mutagenic in an in vitro bacterial reverse mutation (Ames) assay.

Fertility studies with sacituzumab govitecan-hziy have not been conducted. In a repeat-dose toxicity study in cynomolgus monkeys, intravenous administration of sacituzumab govitecan-hziy on Day 1 and Day 4 resulted in endometrial atrophy, uterine hemorrhage, increased follicular atresia of the ovary, and atrophy of vaginal epithelial cells at doses ≥ 60 mg/kg (≥ 6 times the human recommended dose of 10 mg/kg based on body weight).

14 CLINICAL STUDIES

14.1 Locally Advanced or Metastatic Triple-Negative Breast Cancer

ASCENT

Efficacy was evaluated in a multicenter, open-label, randomized study (ASCENT; NCT02574455) conducted in 529 patients with unresectable locally advanced or metastatic triple-negative breast cancer (mTNBC) who had relapsed after at least two prior chemotherapies for breast cancer (one of which could be in the neoadjuvant or adjuvant setting provided progression occurred within a 12 month period). All patients received previous taxane treatment in either the adjuvant, neoadjuvant, or advanced stage unless there was a contraindication or intolerance to taxanes during or at the end of the first taxane cycle. Magnetic resonance imaging (MRI) to determine brain metastases was required prior to enrollment for patients with known or suspected brain metastases. Patients with brain metastases were allowed to enroll up to a pre-defined maximum of 15% of patients in the ASCENT study. Patients with known Gilbert's disease or bone-only disease were excluded.

Patients were randomized (1:1) to receive TRODELVY 10 mg/kg as an intravenous infusion on Days 1 and 8 of a 21-day (n=267) or physician's choice of single agent chemotherapy (n=262). Single agent chemotherapy was determined by the investigator before randomization from one of the following choices: eribulin (n=139), capecitabine (n=33), gemcitabine (n=38), or vinorelbine (n=52).

Patients were treated until disease progression or unacceptable toxicity. The major efficacy outcome was progression-free survival (PFS) in patients without brain metastases at baseline (i.e., BMNeg) as measured by a blinded, independent, centralized review assessed using Response Evaluation Criteria in Solid Tumors (RECIST) v1.1 criteria. Additional efficacy measures included PFS for the full population (all patients with and without brain metastases) and overall survival (OS).

The median age of patients in the full population (n = 529) was 54 years (range: 27 to 82 years); 99.6% were female; 79% were White, 12% were Black/African American; and 81% of patients were < 65 years of age. All patients had an ECOG performance status of 0 (43%) or 1 (57%). Forty-two percent of patients had hepatic metastases, 9% were BRCA1/BRCA2 mutational status positive, and 70% were TNBC at diagnosis. Twelve percent had baseline brain metastases previously treated and stable (n=61; 32 on TRODELVY arm and 29 on single agent chemotherapy arm). Overall, 29% of patients had received prior PD-1/PD-L1 therapy. Thirteen percent of patients in the TRODELVY group in the full population received only 1 prior line of systemic therapy in the metastatic setting.

The efficacy results are summarized in Table 10 and are shown in Figure 1 and Figure 2. Efficacy results for the subgroup of patients who had received only 1 prior line of systemic therapy in the metastatic setting (in addition to having disease recurrence or progression within 12 months of neoadjuvant/adjuvant systemic therapy) were consistent with those who had received at least two prior lines in the metastatic setting.

Table 10: Efficacy Results from ASCENT
 | All Randomized Patients
 | TRODELVY n=267 | Single Agent Chemotherapy n=262
Progression-Free Survival [PFS is defined as the time from the date of randomization to the date of the first radiological disease progression or death due to any cause, whichever comes first.] per BICR
Disease Progression or Death (%) | 190 (71%) | 171 (65%)
Median PFS in months (95% CI) | 4.8 (4.1, 5.8) | 1.7 (1.5, 2.5)
Hazard ratio [Stratified log-rank test adjusted for stratification factors: number of prior chemotherapies, presence of known brain metastases at study entry, and region.] (95% CI) | 0.43 (0.35, 0.54)
p-value | <0.0001
Overall Survival
Deaths (%) | 179 (67%) | 206 (79%)
Median OS in months (95% CI) | 11.8 (10.5, 13.8) | 6.9 (5.9, 7.6)
Hazard ratio (95% CI) | 0.51 (0.41, 0.62)
p-value | <0.0001
CI = Confidence Interval

Figure 1: Kaplan-Meier Plot of PFS by BICR (All Randomized Patients) in ASCENT

Figure 2: Kaplan-Meier Plot of OS (All Randomized Patients) in ASCENT

An exploratory analysis of PFS in patients with previously treated, stable brain metastases showed a stratified HR of 0.65 (95% CI: 0.35, 1.22). The median PFS in the TRODELVY arm was 2.8 months (95% CI: 1.5, 3.9) and the median PFS with single agent chemotherapy was 1.6 months (95% CI: 1.3, 2.9). Exploratory OS analysis in the same population showed a stratified HR of 0.87 (95% CI: 0.47, 1.63). The median OS in the TRODELVY arm was 6.8 months (95% CI: 4.7, 14.1) and the median OS with single agent chemotherapy was 7.4 months (95% CI: 4.7, 11.1).

IMMU-132-01

The efficacy of TRODELVY was evaluated in a multicenter, single-arm, study (NCT01631552) that enrolled 108 patients with metastatic triple-negative breast cancer (mTNBC) who had received at least two prior anticancer therapies for metastatic disease. Patients with bulky disease, defined as a mass > 7 cm, were not eligible. Patients with treated brain metastases not receiving high dose steroids (> 20 mg prednisone or equivalent) for at least four weeks were eligible. Patients with known Gilbert's disease were excluded.

Patients received TRODELVY 10 mg/kg intravenously on Days 1 and 8 of a 21-day treatment cycle. Patients were treated with TRODELVY until disease progression or intolerance to the therapy. Tumor imaging was obtained every 8 weeks, with confirmatory CT/MRI scans obtained 4–6 weeks after an initial partial or complete response, until progression requiring treatment discontinuation. Major efficacy outcome measures were investigator assessed overall response rate (ORR) using RECIST 1.1 and duration of response.

The median age was 55 years (range: 31 to 80 years); 87% of patients were younger than 65 years. The majority of patients were female (99%) and White (76%). At study entry, all patients had an ECOG performance status of 0 (29%) or 1 (71%). Seventy-six percent had visceral disease, 42% had hepatic metastases, 56% had lung/pleura metastases, and 2% had brain metastases. Twelve patients (11%) had Stage IV disease at the time of initial diagnosis.

The median number of prior systemic therapies received in the metastatic setting was 3 (range: 2 to 10). Prior chemotherapies in the metastatic setting included carboplatin or cisplatin (69%), gemcitabine (55%), paclitaxel or docetaxel (53%), capecitabine (51%), eribulin (45%), doxorubicin (24%), vinorelbine (16%), cyclophosphamide (19%), and ixabepilone (8%).

Overall, 98% of patients had received prior taxanes and 86% had received prior anthracyclines either in the (neo)adjuvant or metastatic setting.

Table 11 summarizes the efficacy results.

Table 11: Efficacy results for patients with mTNBC in IMMU-132-01
 | TRODELVY (N=108)
Overall Response Rate [investigator assessment]
ORR (95% CI) | 33.3% (24.6, 43.1)
Complete response | 2.8%
Partial response | 30.6%
Response duration
Number of responders | 36
Median, Months (95% CI) | 7.7 (4.9, 10.8)
Range, Months | 1.9+, 30.4+
% with duration ≥ 6 months | 55.6%
% with duration ≥ 12 months | 16.7%
CI: confidence interval
+: denotes ongoing

14.2 Locally Advanced or Metastatic HR-Positive, HER2-Negative Breast Cancer

TROPiCS-02 Study

The efficacy of TRODELVY was evaluated in a multicenter, open label, randomized study (TROPiCS-02; NCT03901339) conducted in 543 patients with unresectable locally advanced or metastatic HR-positive, HER2-negative (IHC 0, IHC 1+ or IHC 2+/ISH–) breast cancer whose disease has progressed after the following in any setting: a CDK 4/6 inhibitor, endocrine therapy, and a taxane; patients received at least two prior chemotherapies in the metastatic setting (one of which could be in the neoadjuvant or adjuvant setting if recurrence occurred within 12 months).

Patients were randomized (1:1) to receive TRODELVY 10 mg/kg as an intravenous infusion on Days 1 and 8 of a 21 day cycle (n=272) or single agent chemotherapy (n=271). Single agent chemotherapy was determined by the investigator before randomization from one of the following choices: eribulin (n=130), vinorelbine (n=63), gemcitabine (n=56), or capecitabine (n=22). Randomization was stratified by the following factors: prior chemotherapy regimens for metastatic disease (2 vs. 3–4), visceral metastasis (Yes or No), and endocrine therapy in the metastatic setting for at least 6 months (Yes or No).

Patients were treated until disease progression or unacceptable toxicity. Administration of TRODELVY was permitted beyond RECIST-defined disease progression if the patient was clinically stable and considered by the investigator to be deriving clinical benefit. The primary efficacy outcome measure was PFS as determined by BICR per RECIST v1.1. Additional efficacy measures included OS, ORR by BICR, and DOR by BICR.

The median age of patients in the study population was 56 years (range: 27–86 years), 26% of patients were 65 years or over. The majority of patients were female (99%); 67% were White, 4% were Black and 3% were Asian, and 26% were of unknown race. Patients received a median of 7 (range: 3 to 17) prior systemic regimens in any setting and 3 (range: 0 to 8) prior systemic chemotherapy regimens in the metastatic setting. Approximately 42% of patients had 2 prior chemotherapy regimens for treatment of metastatic disease compared to 58% of patients who had 3 to 4 prior chemotherapy regimens and all patients had an ECOG performance status of 0 (45%) or 1 (55%). Ninety-five percent of patients had visceral metastases. Most patients received endocrine therapy in the metastatic setting for ≥ 6 months (86%).

TRODELVY demonstrated a statistically significant improvement in PFS and OS versus single agent chemotherapy.

The efficacy results are summarized in Table 12 and Figure 3 and Figure 4.

Table 12: Efficacy Results from TROPiCS-02
 | All Randomized Patients
 | TRODELVY n=272 | Single Agent Chemotherapy n=271
Progression-Free Survival by BICR [PFS is defined as the time from the date of randomization to the date of the first radiological disease progression or death due to any cause, whichever comes first.]
Median PFS in months (95% CI) | 5.5 (4.2, 7.0) | 4.0 (3.1, 4.4)
Hazard ratio (95% CI) | 0.661 (0.529, 0.826)
p-value [Stratified log-rank test adjusted for stratification factors: prior chemotherapy regimens for metastatic disease (2 vs. 3–4), visceral metastasis (Y/N), and endocrine therapy in the metastatic setting for at least 6 months (Yes or No). BICR = Blinded Independent Central Review; CI = Confidence Interval] | 0.0003
Overall Survival [Second interim OS analysis (conducted when 390 OS events were observed)]
Median OS in months (95% CI) | 14.4 (13.0, 15.7) | 11.2 (10.1, 12.7)
Hazard ratio (95% CI) | 0.789 (0.646, 0.964)
p-value | 0.0200
Objective Response Rate by BICR
Response Rate, % (95% CI) | 21.0 (16.3, 26.3) | 14.0 (10.1, 18.7)
Odds ratio (95% CI) | 1.625 (1.034, 2.555)
p-value | 0.0348
Duration of Response (DOR) by BICR
Median DOR in months (95% CI) | 8.1 (6.7, 9.1) | 5.6 (3.8, 7.9)

Figure 3: Kaplan-Meier Plot of PFS by BICR in TROPiCS-02

Figure 4: Kaplan-Meier Plot of OS in TROPiCS-02

15 REFERENCES

1. "OSHA Hazardous Drugs." OSHA. http://www.osha.gov/SLTC/hazardousdrugs/index.html.

16 HOW SUPPLIED/STORAGE AND HANDLING

TRODELVY (sacituzumab govitecan-hziy) for injection is a sterile, off-white to yellowish lyophilized powder in a single-dose vial. Each TRODELVY vial is individually boxed in a carton:

- NDC 55135-132-01 contains one 180 mg vial

STORAGE AND HANDLING

Store vials in a refrigerator at 2°C to 8°C (36°F to 46°F) in the original carton to protect from light until time of reconstitution. Do not freeze.

TRODELVY is a hazardous drug. Follow applicable special handling and disposal procedures^1.

17 PATIENT COUNSELING INFORMATION

Advise the patient to read the FDA-approved patient labeling (Patient Information)

Neutropenia

Advise patients of the risk of neutropenia. Instruct patients to immediately contact their healthcare provider if they experience fever, chills, or other signs of infection [see Warnings and Precautions (5.1)].

Diarrhea

Advise patients of the risk of diarrhea. Instruct patients to immediately contact their healthcare provider if they experience diarrhea for the first time during treatment; black or bloody stools; symptoms of dehydration such as lightheadedness, dizziness, or faintness; inability to take fluids by mouth due to nausea or vomiting; or inability to get diarrhea under control within 24 hours [see Warnings and Precautions (5.2)].

Hypersensitivity and Infusion-Related Reactions

Inform patients of the risk of serious infusion reactions and anaphylaxis. Instruct patients to immediately contact their healthcare provider if they experience facial, lip, tongue, or throat swelling, urticaria, difficulty breathing, lightheadedness, dizziness, chills, rigors, wheezing, pruritus, flushing, rash, hypotension, or fever that occur during or within 24 hours following the infusion [see Warnings and Precautions (5.3)].

Nausea/Vomiting

Advise patients of the risk of nausea and vomiting. Premedication according to established guidelines with a two or three drug regimen for prevention of chemotherapy-induced nausea and vomiting (CINV) is also recommended. Additional antiemetics, sedatives, and other supportive measures may also be employed as clinically indicated. All patients should receive take-home medications for preventing and treating delayed nausea and vomiting, with clear instructions. Instruct patients to immediately contact their healthcare provider if they experience uncontrolled nausea or vomiting [see Warnings and Precautions (5.4)].

Embryo-Fetal Toxicity

Advise female patients to contact their healthcare provider if they are pregnant or become pregnant. Inform female patients of the risk to a fetus and potential loss of the pregnancy [see Use in Specific Populations (8.1)].

Contraception

Advise female patients of reproductive potential to use effective contraception during treatment and for 6 months after the last dose of TRODELVY [see Use in Specific Populations (8.3)].

Advise male patients with female partners of reproductive potential to use effective contraception during treatment and for 3 months after the last dose of TRODELVY [see Use in Specific Populations (8.3)].

Lactation

Advise women not to breastfeed during treatment and for 1 month after the last dose of TRODELVY [see Use in Specific Populations (8.2)].

Infertility

Advise females of reproductive potential that TRODELVY may impair fertility [see Use in Specific Populations (8.3)].

Manufactured by:

Gilead Sciences, Inc.
333 Lakeside Dr.
Foster City, CA 94404, USA
U.S. License No. 2258

Patient Information
TRODELVY® (troh-DELL-vee)
(sacituzumab govitecan-hziy)
for injection, for intravenous use

What is the most important information I should know about TRODELVY?
TRODELVY can cause serious side effects, including:

- Low white blood cell count (neutropenia). Low white blood cell counts are common with TRODELVY and can sometimes be severe and lead to infections that can be life-threatening or cause death as early as the first cycle of treatment. Your healthcare provider should check your blood cell counts during treatment with TRODELVY and may give a medicine to help prevent low blood cell count starting in the first cycle of treatment if you have an increased risk for developing low white blood cell count with a fever (febrile neutropenia). If your white blood cell count is too low, your healthcare provider may need to delay treatment or lower your dose of TRODELVY, give you a medicine to treat low blood cell count, or in some cases may permanently stop TRODELVY. Your healthcare provider may need to give you antibiotic medicines if you develop fever while your white blood cell count is low.
  Call your healthcare provider right away if you develop any of the following signs of infection during treatment with TRODELVY:

- fever
- chills
- cough

- shortness of breath
- burning or pain when you urinate

- Severe diarrhea. Diarrhea is common with TRODELVY and can also be severe. Severe diarrhea can lead to loss of too much body fluid (dehydration) and kidney problems. Your healthcare provider should monitor you for diarrhea and give you medicine as needed to help control your diarrhea. If you lose too much body fluid, your healthcare provider may need to give you fluids and electrolytes to replace body salts. If you develop diarrhea during treatment with TRODELVY, your healthcare provider should check to see if diarrhea may be caused by an infection. Your healthcare provider may decrease your dose, delay treatment, or permanently stop TRODELVY if your diarrhea is severe and cannot be controlled with anti-diarrheal medicines.
  Call your healthcare provider right away:
  - the first time that you get diarrhea during treatment with TRODELVY
  - if you have black or bloody stools
  - if you have symptoms of losing too much body fluid and body salts, such as lightheadedness, dizziness, or faintness
  - if you are unable to take fluids by mouth due to nausea or vomiting
  - if you are not able to get your diarrhea under control within 24 hours

What is TRODELVY?
TRODELVY is a prescription medicine used to treat adults with:

- a type of breast cancer called triple-negative breast cancer (TNBC), which is estrogen and progesterone hormone receptor (HR)-negative and human epidermal growth factor receptor 2 (HER2)-negative. TRODELVY may be used:
  - when your breast cancer has spread to other parts of the body (metastatic) or cannot be removed by surgery,
    and
  - if you previously received two or more prior treatments, including at least one treatment for metastatic disease.
- a type of breast cancer that is HR-positive and HER2-negative. TRODELVY may be used:
  - when your breast cancer has spread to other parts of the body or cannot be removed by surgery,
    and
    if you previously received endocrine therapy and at least two additional treatments for metastatic disease.

It is not known if TRODELVY is safe and effective in people with moderate or severe liver problems.
It is not known if TRODELVY is safe and effective in children.

Do not receive TRODELVY if you have had a severe allergic reaction to TRODELVY. Ask your healthcare provider if you are not sure.

Before receiving TRODELVY, tell your healthcare provider about all of your medical conditions, including if you:

- have been told that you carry a gene for uridine diphosphate-glucuronosyl transferase 1A1 (UGT1A1)*28. People who carry this gene have an increased risk of getting side effects with TRODELVY, especially low white blood cell counts, a fever while your white blood cell count is low, and low red blood cell counts. See "What is the most important information I should know about TRODELVY?"
- have liver problems.
- are pregnant or plan to become pregnant. TRODELVY can harm your unborn baby. Your healthcare provider should check to see if you are pregnant before you start receiving TRODELVY.
  - Females who can become pregnant should use effective birth control during treatment and for 6 months after your last dose of TRODELVY. Talk to your healthcare provider about birth control choices that may be right for you during this time. Tell your healthcare provider right away if you become pregnant during treatment with TRODELVY.
  - Males with a female partner who can become pregnant should use effective birth control during treatment and for 3 months after your last dose of TRODELVY.
- are breastfeeding or plan to breastfeed. It is not known if TRODELVY passes into your breastmilk and can harm your baby. Do not breastfeed during treatment and for 1 month after your last dose of TRODELVY.

Tell your healthcare provider about all the medicines you take, including prescription and over-the-counter medicines, vitamins, and herbal supplements. Certain medicines may affect the way TRODELVY works.

How will I receive TRODELVY?

- Your healthcare provider will give you TRODELVY into your vein through an intravenous (IV) line.
- TRODELVY is given 1 time each week, on Day 1 and on Day 8 of a 21-day treatment cycle.
- You will receive the first dose of TRODELVY over 3 hours. If you tolerate the first dose well, future doses may be given over 1 to 2 hours.
- Before each dose of TRODELVY, you will receive medicines to help prevent infusion-related reactions, and nausea and vomiting.
- You will be monitored for side effects during and for at least 30 minutes after you receive each infusion of TRODELVY.
- Your healthcare provider may slow down or temporarily stop your infusion of TRODELVY if you have an infusion-related reaction, or permanently stop TRODELVY if you have a life-threatening infusion-related reaction.
- Your healthcare provider will decide how long you will continue to receive TRODELVY.

What are the possible side effects of TRODELVY?
TRODELVY can cause serious side effects, including:

- See "What is the most important information I should know about TRODELVY?"
- Allergic and infusion-related reactions. TRODELVY can cause serious or life-threatening allergic and infusion-related reactions. Tell your healthcare provider or nurse right away if you get any of the following symptoms of an allergic or infusion-related reaction during your infusion of TRODELVY or within 24 hours after you receive a dose of TRODELVY:

- swelling of your face, lips, tongue, or throat
- hives
- skin rash, itching, or flushing of your skin
- fever

- difficulty breathing or wheezing
- lightheadedness, dizziness, feeling faint or pass out
- chills or shaking chills (rigors)

- Nausea and vomiting. Nausea and vomiting are common with TRODELVY and can sometimes be severe. Before each dose of TRODELVY, you will receive medicines to help prevent nausea and vomiting. You should be given medicines to take home with you, along with instructions about how to take them to help prevent and treat any nausea and vomiting after you receive TRODELVY. Call your healthcare provider right away if you have nausea or vomiting that is not controlled with the medicines prescribed for you. Your healthcare provider may decide to decrease your dose, delay treatment, or permanently stop TRODELVY if your nausea and vomiting is severe and cannot be controlled with anti-nausea medicines.

The most common side effects of TRODELVY include:

- decreased white blood cell (leukocyte and lymphocyte) and red blood cell counts
- feeling tired or weak
- hair loss
- constipation
- increased sugar levels in the blood
- decreased protein levels (albumin) in the blood

- decreased appetite
- changes in kidney function test
- increased levels of enzyme called alkaline phosphatase in the blood (test for liver or bone problems)
- decreased levels of magnesium, potassium, and sodium in the blood

TRODELVY may cause fertility problems in females, which could affect your ability to have a baby. Talk to your healthcare provider if fertility is a concern for you.
These are not all of the possible side effects of TRODELVY.
Call your doctor for medical advice about side effects. You may report side effects to FDA at 1-800-FDA-1088.

General information about the safe and effective use of TRODELVY.
Medicines are sometimes prescribed for purposes other than those listed in a Patient Information leaflet. You can ask your pharmacist or healthcare provider for information about TRODELVY that is written for health professionals.

What are the ingredients in TRODELVY?
Active ingredient: sacituzumab govitecan-hziy
Inactive ingredients: 2-(N-morpholino) ethane sulfonic acid (MES), polysorbate 80 and trehalose
Manufactured by: Gilead Sciences, Inc., 333 Lakeside Dr., Foster City, CA 94404, USA
U.S. License No. 2258
761115-GS-010
For more information about TRODELVY, go to www.TRODELVY.com or call 1-888-983-4668.

The Patient Information has been approved by the U.S. Food and Drug Administration.

Revised: 03/2025

PRINCIPAL DISPLAY PANEL - 180 mg Vial Label

NDC 55135-132-01

Rx only

TRODELVY®
sacituzumab govitecan-hziy
For injection

180 mg per vial

For intravenous infusion only

Warning: Hazardous Drug

Single-dose vial
Discard unused portion

90370103

PRINCIPAL DISPLAY PANEL - 180 mg Vial Box

NDC 55135-132-01

Rx only

TRODELVY®
sacituzumab govitecan-hziy
For injection

180 mg per vial

For intravenous infusion only

Warning: Hazardous Drug

Reconstitute and dilute
immediately prior to use

Single-dose vial
Discard unused portion

1 Vial